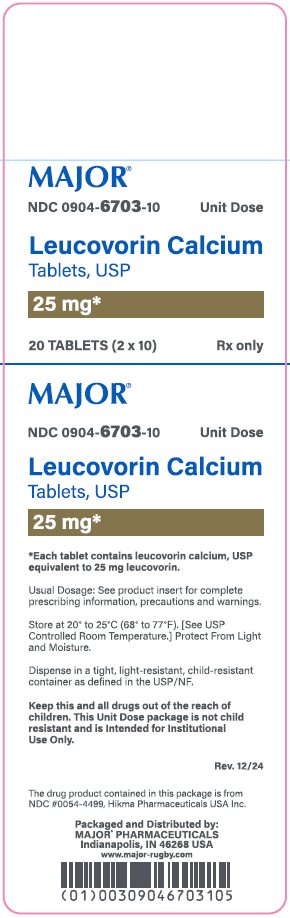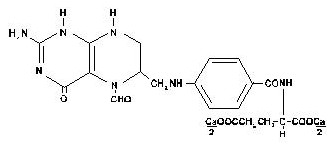 DRUG LABEL: Leucovorin Calcium
NDC: 0904-6703 | Form: TABLET
Manufacturer: Major Pharmaceuticals
Category: prescription | Type: HUMAN PRESCRIPTION DRUG LABEL
Date: 20260219

ACTIVE INGREDIENTS: LEUCOVORIN CALCIUM 25 mg/1 1
INACTIVE INGREDIENTS: SILICON DIOXIDE; CROSCARMELLOSE SODIUM; D&C YELLOW NO. 10; MAGNESIUM STEARATE; MICROCRYSTALLINE CELLULOSE; POVIDONE, UNSPECIFIED; STARCH, CORN

Leucovorin Calcium Tablets USP, 5 mg, 10 mg, 15 mg, and 25 mg

DESCRIPTION

Leucovorin calcium tablets, USP contain either 5 mg, 10 mg, 15 mg or 25 mg leucovorin as the calcium salt of N-[4-[[(2-amino-5-formyl-1,4,5,6,7,8-hexahydro-4-oxo-6-pteridinyl)methyl] amino]benzoyl]-L-glutamic acid. This is equivalent to either 5.4 mg, 10.8 mg, 16.21 mg or 27.01 mg of anhydrous leucovorin calcium, USP, respectively. In addition, each tablet contains the following inactive ingredients: colloidal silicon dioxide, croscarmellose sodium, D&C yellow #10 (15 mg and 25 mg), magnesium stearate, microcrystalline cellulose, povidone and pregelatinized starch.

Leucovorin is a water soluble form of reduced folate in the folate group; it is useful as an antidote to drugs which act as folic acid antagonists. These tablets are intended for oral administration only.

The structural formula of leucovorin calcium is:

C20H21CaN7O7 M.W. 511.51

CLINICAL PHARMACOLOGY

Leucovorin is a racemic mixture of the diastereoisomers of the 5-formyl derivative of tetrahydrofolic acid. The biologically active compound of the mixture is the (-)-L-isomer, known as Citrovorum factor, or (-)-folinic acid. Leucovorin does not require reduction by the enzyme dihydrofolate reductase in order to participate in reactions utilizing folates as a source of “one-carbon” moieties. Following oral administration, leucovorin is rapidly absorbed and enters the general body pool of reduced folates. The increase in plasma and serum folate activity (determined microbiologically with Lactobacillus casei) seen after oral administration of leucovorin is predominantly due to 5-methyltetrahydrofolate.

Twenty normal men were given a single, oral 15 mg dose (7.5 mg/m^2) of leucovorin calcium and serum folate concentrations were assayed with L. casei. Mean values observed (± one standard error) were:

a) Time to peak serum folate concentration: 1.72 ± 0.08 hours,

b) Peak serum folate concentration achieved: 268 ± 18 ng/mL,

c) Serum folate half-disappearance time: 3.5 hours.

Oral tablets yielded areas under the serum folate concentration-time curves (AUCs) that were 12% greater than equal amounts of leucovorin given intramuscularly and equal to the same amounts given intravenously.

Oral absorption of leucovorin is saturable at doses above 25 mg. The apparent bioavailability of leucovorin was 97% for 25 mg, 75% for 50 mg and 37% for 100 mg.

INDICATIONS AND USAGE

Leucovorin is indicated to diminish the toxicity and counteract the effects of impaired methotrexate elimination and of inadvertent overdosages of folic acid antagonists.

CONTRAINDICATIONS

Leucovorin is improper therapy for pernicious anemia and other megaloblastic anemias secondary to the lack of vitamin B12. A hematologic remission may occur while neurologic manifestations continue to progress.

WARNINGS

In the treatment of accidental overdosage of folic acid antagonists, leucovorin should be administered as promptly as possible. As the time interval between antifolate administration (e.g., methotrexate) and leucovorin rescue increases, leucovorin’s effectiveness in counteracting hematologic toxicity decreases.

Monitoring of the serum methotrexate concentration is essential in determining the optimal dose and duration of treatment with leucovorin.

Delayed methotrexate excretion may be caused by a third space fluid accumulation (i.e., ascites, pleural effusion), renal insufficiency, or inadequate hydration. Under such circumstances, higher doses of leucovorin or prolonged administration may be indicated. Doses higher than those recommended for oral use must be given intravenously.

Leucovorin may enhance the toxicity of fluorouracil. Deaths from severe enterocolitis, diarrhea, and dehydration have been reported in elderly patients receiving weekly leucovorin and fluorouracil.^1 Concomitant granulocytopenia and fever were present in some but not all of the patients.

The concomitant use of leucovorin with trimethoprim-sulfamethoxazole for the acute treatment of Pneumocystis carinii pneumonia in patients with HIV infection was associated with increased rates of treatment failure and mortality in a placebo-controlled study.

PRECAUTIONS

General

Parenteral administration is preferable to oral dosing if there is a possibility that the patient may vomit or not absorb the leucovorin. Leucovorin has no effect on other established toxicities of methotrexate such as the nephrotoxicity resulting from drug and/or metabolite precipitation in the kidney.

Drug Interactions

Folic acid in large amounts may counteract the antiepileptic effect of phenobarbital, phenytoin and primidone, and increase the frequency of seizures in susceptible children.

Preliminary animal and human studies have shown that small quantities of systemically administered leucovorin enter the CSF primarily as 5-methyltetrahydrofolate and, in humans, remain 1 to 3 orders of magnitude lower than the usual methotrexate concentrations following intrathecal administration. However, high doses of leucovorin may reduce the efficacy of intrathecally administered methotrexate.

Leucovorin may enhance the toxicity of fluorouracil [see WARNINGS].

Pregnancy

Teratogenic Effects

Animal reproduction studies have not been conducted with leucovorin. It is also not known whether leucovorin can cause fetal harm when administered to a pregnant woman or can affect reproduction capacity. Leucovorin should be given to a pregnant woman only if clearly needed.

Nursing Mothers

It is not known whether this drug is excreted in human milk. Because many drugs are excreted in human milk, caution should be exercised when leucovorin is administered to a nursing mother.

Pediatric Use

See Drug Interactions subsection.

ADVERSE REACTIONS

Allergic sensitization, including anaphylactoid reactions and urticaria, has been reported following the administration of both oral and parenteral leucovorin.

OVERDOSAGE

Excessive amounts of leucovorin may nullify the chemotherapeutic effect of folic acid antagonists.

DOSAGE AND ADMINISTRATION

Leucovorin calcium tablets are intended for oral administration. Because absorption is saturable, oral administration of doses greater than 25 mg is not recommended.

Impaired Methotrexate Elimination or Inadvertent Overdosage

Leucovorin rescue should begin as soon as possible after an inadvertent overdosage and within 24 hours of methotrexate administration when there is delayed excretion [see WARNINGS]. Leucovorin 15 mg (10 mg/m^2) should be administered IM, IV, or PO every 6 hours until the serum methotrexate level is less than 10^-8 M. In the presence of gastrointestinal toxicity, nausea, or vomiting, leucovorin should be administered parenterally.

Serum creatinine and methotrexate levels should be determined at 24-hour intervals. If the 24-hour serum creatinine has increased 50% over baseline or if the 24-hour methotrexate level is greater than 5 x 10^-6 M or the 48-hour level is greater than 9 x 10^-7 M, the dose of leucovorin should be increased to 150 mg (100 mg/m^2) IV every 3 hours until the methotrexate level is less than 10^-8 M. Doses greater than 25 mg should be given parenterally [see CLINICAL PHARMACOLOGY].

Hydration (3 L/d) and urinary alkalinization with sodium bicarbonate should be employed concomitantly. The bicarbonate dose should be adjusted to maintain the urine pH at 7.0 or greater.

The recommended dose of leucovorin to counteract hematologic toxicity from folic acid antagonists with less affinity for mammalian dihydrofolate reductase than methotrexate (i.e., trimethoprim, pyrimethamine) is substantially less, and 5 to 15 mg of leucovorin per day has been recommended by some investigators.

Patients who experience delayed early methotrexate elimination are likely to develop reversible non-oliguric renal failure. In addition to appropriate leucovorin therapy, these patients require continuing hydration and urinary alkalinization, and close monitoring of fluid and electrolyte status, until the serum methotrexate level has fallen below 0.05 micromolar and the renal failure has resolved.

Some patients will have abnormalities in methotrexate elimination or renal function following methotrexate administration, which are significant but less severe. These abnormalities may or may not be associated with significant clinical toxicity. If significant clinical toxicity is observed, leucovorin rescue should be extended for an additional 24 hours (total 14 doses over 84 hours) in subsequent courses of therapy. The possibility that the patient is taking other medications which interact with methotrexate (e.g., medications which may interfere with methotrexate elimination or binding to serum albumin) should always be reconsidered when laboratory abnormalities or clinical toxicities are observed.

How Supplied/Storage and Handling

Leucovorin Calcium Tablets, USP

25 mg tablets are supplied as an yellow, round, slightly biconvex tablet; scored on one side and product identification “54 013” debossed on the other side.

Cartons of 20 tablets (10 tablets each blister pack x 2), NDC 0904-6703-10

WARNING: This Unit Dose package is not child resistant and is Intended for Institutional Use Only. Keep this and all drugs out of the reach of children.

Store at 20° to 25°C (68° to 77°F). [See USP Controlled Room Temperature.]

Protect From Light and Moisture.

References

1. Grem JL, Shoemaker DD, Petrelli NJ, Douglas HO. Severe and fatal toxic effects observed in treatment with high- and low-dose leucovorin plus 5-fluorouracil for colorectal carcinoma. Cancer Treat Rep 1987;71:1122.
2. Link MP, Goorin AM, Miser AW et al. The effect of adjuvant chemotherapy on relapse-free survival in patients with osteosarcoma of the extremity. N Engl J Med 1986;314:1600-1606.

Distributed by: Hikma
Pharmaceuticals USA Inc.
Berkeley Heights, NJ 07922

Packaged and Distributed by:

MAJOR® PHARMACEUTICALS

Indianapolis, IN 46268 USA

Refer to package label for Distributor's NDC Number

C50000693/01

Revised June 2023

Package/Label Display Panel

MAJOR®

NDC 0904-6703-10

Unit Dose

Leucovorin Calcium

Tablets, USP

25 mg*

20 TABLETS (2 x 10)

Rx only